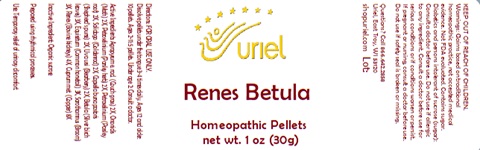 DRUG LABEL: Renes Betula
NDC: 48951-8426 | Form: PELLET
Manufacturer: Uriel Pharmacy Inc.
Category: homeopathic | Type: HUMAN OTC DRUG LABEL
Date: 20241210

ACTIVE INGREDIENTS: ELYMUS REPENS TOP 3 [hp_X]/1 1; ONONIS REPENS ROOT 3 [hp_X]/1 1; PARSLEY 3 [hp_X]/1 1; CAPSELLA BURSA-PASTORIS 3 [hp_X]/1 1; ARCTOSTAPHYLOS UVA-URSI LEAF 3 [hp_X]/1 1; SOLIDAGO VIRGAUREA FLOWERING TOP 3 [hp_X]/1 1; BETULA PUBESCENS LEAF 4 [hp_X]/1 1; EQUISETUM ARVENSE TOP 4 [hp_X]/1 1; CYTISUS SCOPARIUS FLOWERING TOP 4 [hp_X]/1 1; PORK KIDNEY 4 [hp_X]/1 1; COPPER 9 [hp_X]/1 1
INACTIVE INGREDIENTS: SUCROSE

Renes Betula

INDICATIONS AND USAGE

Directions: FOR ORAL USE ONLY.

DOSAGE AND ADMINISTRATION

Dissolve pellets under the tongue 3-4 times daily. Ages 12 and older: 10 pellets. Ages 2-11: 5 pellets. Under age 2: Consult a doctor.

ACTIVE INGREDIENT

Active Ingredients: Agropyrum e. rad. (Couch grass) 2X, Ononidis (Moth) 2X, Petroselinium (Parsley herb) 2X, Petroselinium (Parsley root) 2X, Solidago (Goldenrod) 2X, Capsella bursa pastoris (Shepherd’s purse) 2X, Uva ursi (Bearberry) 2X, Betula (Silver birch leaves) 3X, Equisetum (Common horsetail) 3X, Sarothamnus (Broom) 3X, Renes (Bovine kidneys) 4X, Cuprum met. (Copper) 8X

Inactive Ingredient: Sucrose

Prepared using rhythmical processes.

PURPOSE

Use: Temporary relief of urinary discomfort.

KEEP OUT OF REACH OF CHILDREN.

QUESTIONS

Questions? Call 866.642.2858 Uriel, East Troy, WI 53120 shopuriel.com Lot:

WARNINGS

Warnings: Claims based on traditional homeopathic practice, not accepted medical evidence. Not FDA evaluated. Contains sugar. Diabetics and persons intolerant of sucrose (sugar): Consult a doctor before use. Do not use if allergic to any ingredient. Consult a doctor before use for serious conditions or if conditions worsen or persist. If pregnant or nursing, consult a doctor before use. Do not use if safety seal is broken or missing.